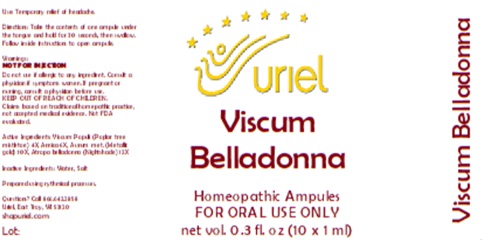 DRUG LABEL: Viscum Belladonna
NDC: 48951-9061 | Form: LIQUID
Manufacturer: Uriel Pharmacy Inc.
Category: homeopathic | Type: HUMAN OTC DRUG LABEL
Date: 20260116

ACTIVE INGREDIENTS: VISCUM ALBUM FRUITING TOP 4 [hp_X]/1 mL; ARNICA MONTANA 6 [hp_X]/1 mL; GOLD 10 [hp_X]/1 mL; ATROPA BELLADONNA 12 [hp_X]/1 mL
INACTIVE INGREDIENTS: WATER; SODIUM CHLORIDE

Viscum Belladonna

PURPOSE

Use: Temporary relief of headache.

INDICATIONS AND USAGE

FOR ORAL USE ONLY

DOSAGE AND ADMINISTRATION

Directions: Take the contents of one ampule under the tongue and hold for 30 seconds, then swallow. Follow inside instructions to open ampule.

Warnings:
Do not use if allergic to any ingredient. Consult a physician if symptoms worsen. If pregnant or nursing, consult a physician before use.
KEEP OUT OF REACH OF CHILDREN.
Claims based on traditional homepathic practice, not accepted medical evidence. Not FDA evaluated.

KEEP OUT OF REACH OF CHILDREN.

ACTIVE INGREDIENT

Active Ingredients: Viscum Populi (Poplar tree mistletoe) 4X, Arnica 6X, Aurum met. (Metallic gold) 10X, Atropa belladonna (Nightshade) 12X

Inactive Ingredients: Water, Salt

Questions? Call 866.642.2858
Uriel, East Troy, WI 53120
www.urielpharmacy.com